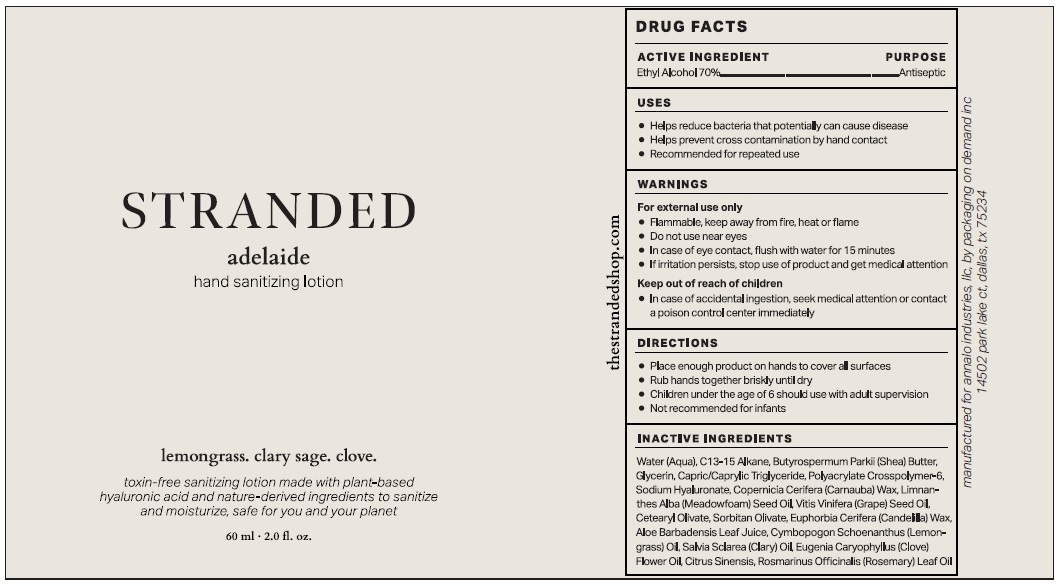 DRUG LABEL: STRANDED Hand Sanitizing
NDC: 82246-000 | Form: LOTION
Manufacturer: Annalo Industries, LLC
Category: otc | Type: HUMAN OTC DRUG LABEL
Date: 20211125

ACTIVE INGREDIENTS: ALCOHOL 0.7 mL/1 mL
INACTIVE INGREDIENTS: WATER; C13-15 ALKANE; SHEA BUTTER; GLYCERIN; MEDIUM-CHAIN TRIGLYCERIDES; AMMONIUM ACRYLOYLDIMETHYLTAURATE, DIMETHYLACRYLAMIDE, LAURYL METHACRYLATE AND LAURETH-4 METHACRYLATE COPOLYMER, TRIMETHYLOLPROPANE TRIACRYLATE CROSSLINKED (45000 MPA.S); HYALURONATE SODIUM; CARNAUBA WAX; MEADOWFOAM SEED OIL; GRAPE SEED OIL; CETEARYL OLIVATE; SORBITAN OLIVATE; CANDELILLA WAX; ALOE VERA LEAF; WEST INDIAN LEMONGRASS OIL; CLARY SAGE OIL; CLOVE OIL; CITRUS SINENSIS FRUIT OIL; ROSEMARY OIL

STRANDED hand sanitizing lotion

ACTIVE INGREDIENT

Ethyl Alcohol 70%

PURPOSE

Antiseptic

USES

- Helps reduce bacteria that potentially can cause disease
- Helps prevent cross contamination by hand contact
- Recommended for repeated use

WARNINGS

For external use only.

- Flammable, keep away from fire, heat, or flame
- Do not use near eyes
- In case of eye contact, flush with water for 15 minutes
- If irritation persists, stop use of product and get medical attention

Keep out of reach of children

- In case of accidental ingestion, seek medical attention or contact a poison control center immediately

DIRECTIONS

- Place enough product on hands to cover all surfaces
- Rub hands together briskly until dry
- Children under the age of 6 should use with adult supervision
- Not recommended for infants

INACTIVE INGREDIENTS

Water (Aqua), C13-15 Alkane, Butyrospermum Parkii (Shea) Butter, Glycerin, Capric/Caprylic Triglyceride, Polyacrylate Crosspolymer-6, Sodium Hyaluronate, Copernica Cerifera (Carnauba) Wax, Limnanthes Alba (Meadowfoam) Seed Oil, Vitis Vinifera (Grape) Seed Oil, Cetearyl Olivate, Sorbitan Olivate, Euphorbia Cerifera (Candelilla) Wax, Aloe Barbadensis Leaf Juice, Cymbopogon Schoenanthus (Lemon-grass) Oil, Salvia Sclarea (Clary) Oil, Eugenia Caryophyllus (Clove) Flower Oil, Citrus Sinensis, Rosmarinus Officinalis (Rosemary) Leaf Oil

adelaide

lemongrass, clary sage. clove.

toxin-free sanitizing lotion made with plant-based hyaluronic acid and nature-derived ingredients to sanitize and moisturize, safe for you and your planet

manufactured for annalo industries, llc, by packaging on demand inc
14502 park lake ct, dallas, tx 75234